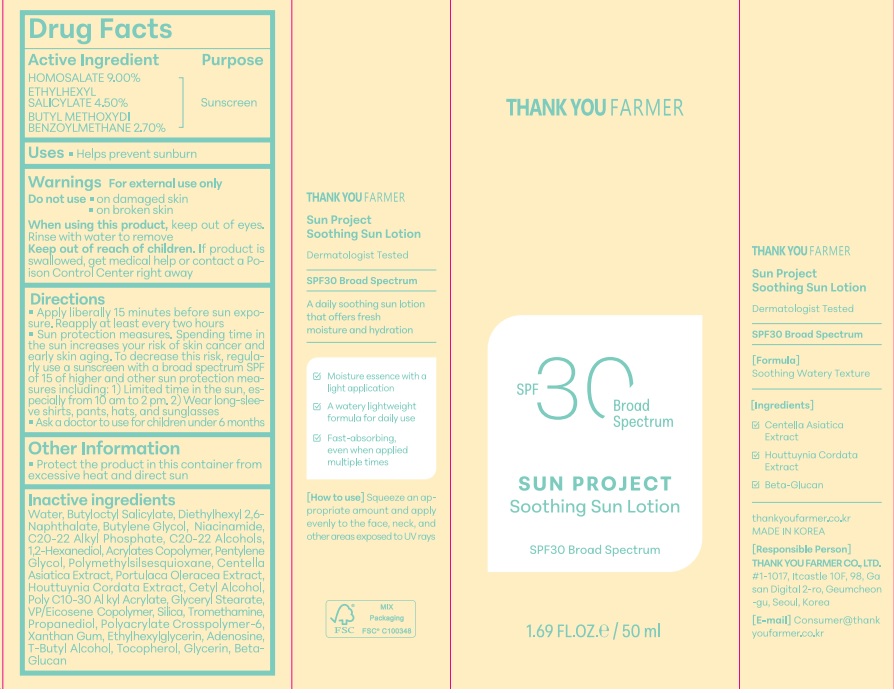 DRUG LABEL: THANK YOU FARMER Sun Project Soothing
NDC: 70618-030 | Form: CREAM
Manufacturer: THANK YOU FARMER CO., LTD
Category: otc | Type: HUMAN OTC DRUG LABEL
Date: 20260113

ACTIVE INGREDIENTS: HOMOSALATE 4.5 g/50 mL; OCTISALATE 2.25 g/50 mL; AVOBENZONE 1.35 g/50 mL
INACTIVE INGREDIENTS: BUTYLOCTYL SALICYLATE; VINYLPYRROLIDONE/EICOSENE COPOLYMER; ETHYLHEXYLGLYCERIN; C20-22 ALCOHOLS; SILICON DIOXIDE; XANTHAN GUM; PURSLANE; CENTELLA ASIATICA TRITERPENOIDS; TOCOPHEROL; GLYCERIN; BUTYLENE GLYCOL; 1,3-BETA-GLUCAN SYNTHASE COMPONENT FKS1; DIETHYLHEXYL 2,6-NAPHTHALATE; POLYMETHYLSILSESQUIOXANE (11 MICRONS); BEHENYL ACRYLATE POLYMER; TERT-BUTYL ALCOHOL; BUTYL ACRYLATE/METHYL METHACRYLATE/METHACRYLIC ACID COPOLYMER (18000 MW); WATER; ADENOSINE; HOUTTUYNIA CORDATA FLOWERING TOP; NIACINAMIDE; C20-22 ALKYL PHOSPHATE; PROPANEDIOL; CETYL ALCOHOL; TROMETHAMINE; GLYCERYL STEARATE SE; AMMONIUM ACRYLOYLDIMETHYLTAURATE; 1,2-HEXANEDIOL; PENTYLENE GLYCOL

Active Ingredient

Active Ingredient-HOMOSALATE 9%, ETHYLHEXYL SALICYLATE-4.5%, BUTYL METHOXYDIBENZOYLMETHANE-2.7%

Purpose

Purpose-Sunscreen, Uses-Helps prevent sunburn

When using this product, keep out of eyes. Rinse with water to remove

Keep Out Of Reach of Children-Keep Out Of Reach of Children- If product is swallowed, get medical help or contact a Poison Control Center right away

Ask a doctor to use for children under 6 months

Do not use on damaged skin, on broken skin

Warning

Warning-For external use only

Inactive Ingredients

Inactive Ingredients-WATER, BUTYLOCTYL SALICYLATE, DIETHYLHEXYL 2,6-NAPHTHALATE, BUTYLENE GLYCOL,NIACINAMIDE, C20-22 ALKYL PHOSPHATE, C20-22 ALCOHOLS, 1,2-HEXANEDIOL, POLYMETHYLSILSESQUIOXANE, ACRYLATES COPOLYMER, PENTYLENE GLYCOL, CETYL ALCOHOL, POLY C10-30 ALKYL ACRYLATE, SILICA, VP/EICOSENE COPOLYMER, GLYCERYL STEARATE, TROMETHAMINE, PROPANEDIOL, POLYACRYLATE CROSSPOLYMER-6, XANTHAN GUM, ETHYLHEXYLGLYCERIN, ADENOSINE, PORTULACA OLERACEA EXTRACT, CENTELLA ASIATICA EXTRACT, HOUTTUYNIA CORDATA EXTRACT, T-BUTYL ALCOHOL, TOCOPHEROL, GLYCERIN, BETA-GLUCAN

Other Safety Information-Protect the product in this container from excessive heat and direct sun

Incations & usage

Incations & usage-Helps prevent sunburn

Dosage & administration

Dosage & administration -Apply liberally 15 minutes before sun exposure. Reapply at least every two hours

PACKAGE LABEL

Package Label Principal Display Panel-Thank you Farmer SPF30 Broad Spectrum, Sun Project Soothing Sun Lotion SPF30 Broad Spectrum 1.69FL.OZ/50ML